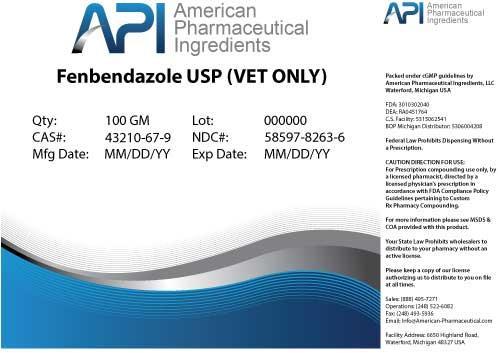 DRUG LABEL: Fenbendazole
NDC: 58597-8263 | Form: POWDER
Manufacturer: AMERICAN PHARMACEUTICAL INGREDIENTS LLC
Category: other | Type: BULK INGREDIENT
Date: 20140425

ACTIVE INGREDIENTS: Fenbendazole 1 g/1 g

Fenbendazole